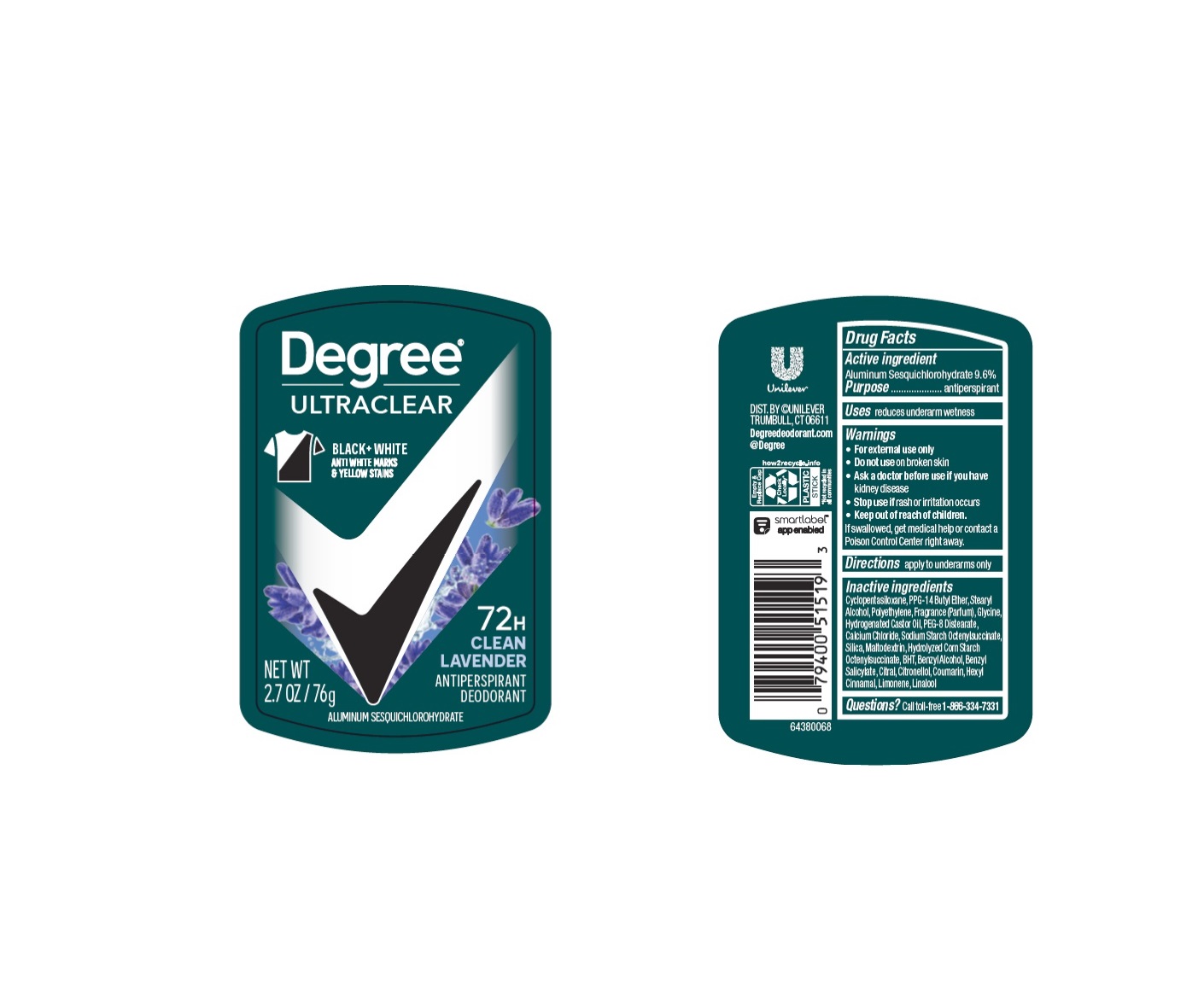 DRUG LABEL: Degree
NDC: 64942-2313 | Form: STICK
Manufacturer: Conopco Inc. d/b/a/ Unilever
Category: otc | Type: HUMAN OTC DRUG LABEL
Date: 20240613

ACTIVE INGREDIENTS: ALUMINUM SESQUICHLOROHYDRATE 9.6 g/100 g
INACTIVE INGREDIENTS: COUMARIN; LINALOOL, (+/-)-; .ALPHA.-HEXYLCINNAMALDEHYDE; .BETA.-CITRONELLOL, (R)-; LIMONENE, (+)-; GLYCINE; HYDROGENATED CASTOR OIL; CALCIUM CHLORIDE; CYCLOMETHICONE 5; BUTYLATED HYDROXYTOLUENE; HIGH DENSITY POLYETHYLENE; PEG-8 DISTEARATE; MALTODEXTRIN; PPG-14 BUTYL ETHER; STEARYL ALCOHOL; SILICON DIOXIDE; BENZYL SALICYLATE; CITRAL; BENZYL ALCOHOL

Degree Ultraclear Black + White Clean Lavender Antiperspirant Deodorant

Drug Facts

Active ingredient

Aluminum Sesquichlorohydrate (9.6%)

Purpose

antiperspirant

Uses

reduces underarm wetness

Warnings

• For external use only.
• Do not use on broken skin .
• Ask a doctor before use if you have kidney disease.
• Stop use if rash or irritation occurs.

• Keep out of reach of children.

If swallowed, get medical help or contact a Poison Control Center right away.

Directions

apply to underarms only

Inactive ingredients

Cyclopentasiloxane, PPG-14 Butyl Ether, Stearyl Alcohol, Polyethylene, Fragrance (Parfum), Glycine, Hydrogenated Castor Oil, PEG-8 Distearate, Calcium Chloride, Sodium Starch Octenylsuccinate, Silica, Maltodextrin, Hydrolyzed Corn Starch Octenylsuccinate, BHT, Benzyl Alcohol, Benyl Salicylate, Citral, Citronellol, Coumarin, Hexyl Cinnamal, Limonene, Linalool

Questions?

Call toll-free 1-866-334-7331